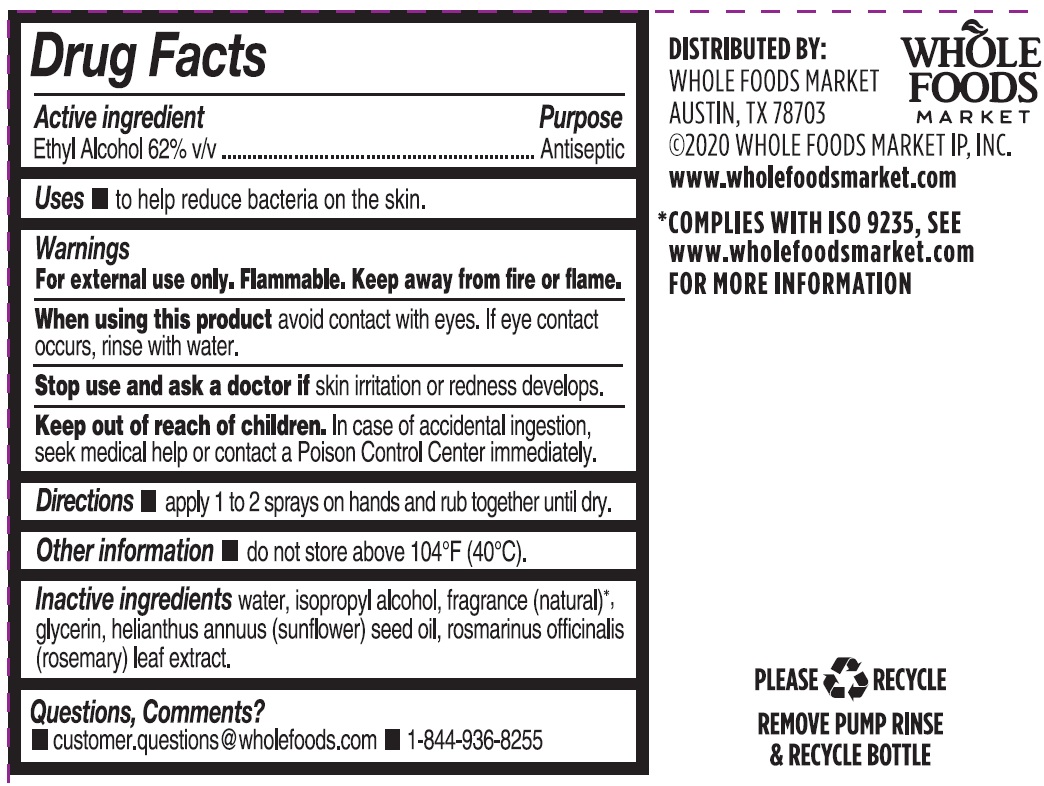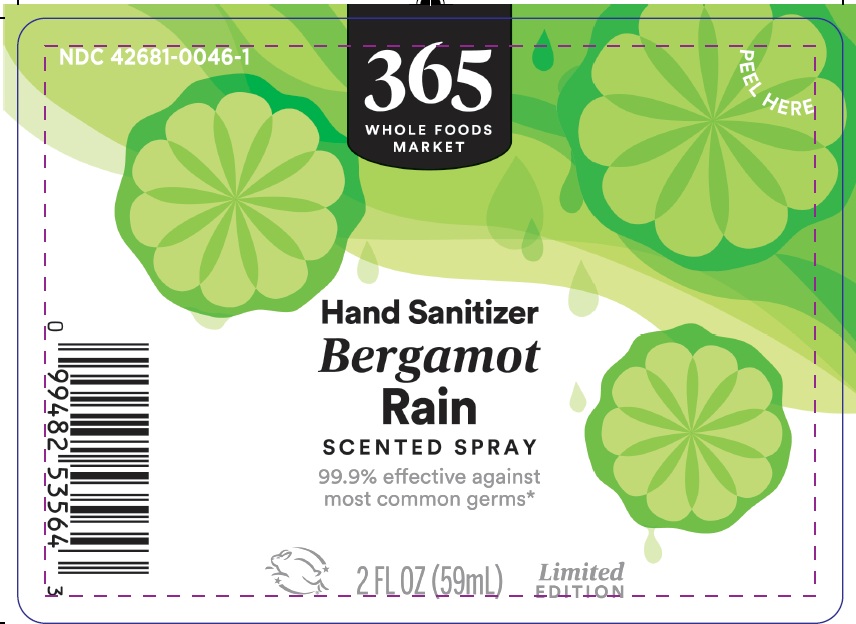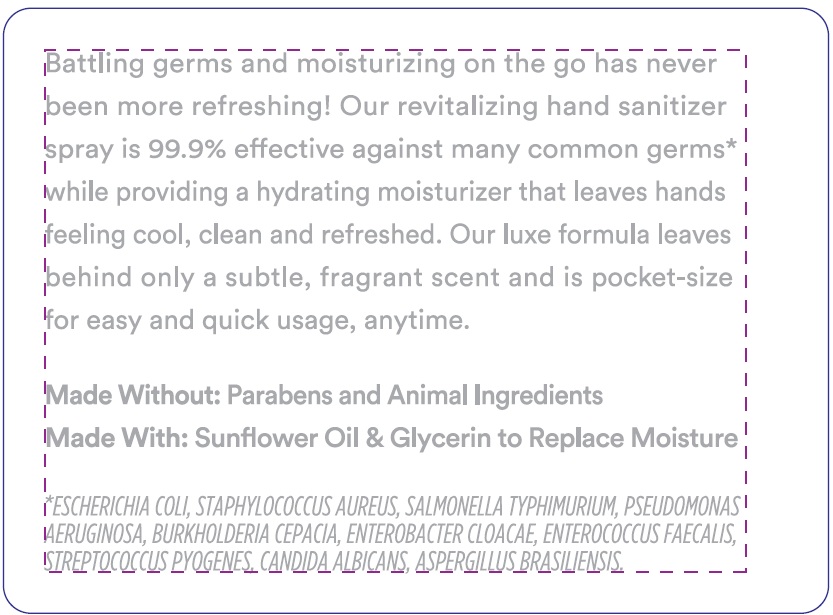 DRUG LABEL: 365 Whole Foods Market Refreshing Hand Sanitizer Bergamot Rain
NDC: 42681-0046 | Form: SPRAY
Manufacturer: Whole Foods Market, Inc.
Category: otc | Type: HUMAN OTC DRUG LABEL
Date: 20250815

ACTIVE INGREDIENTS: ALCOHOL 62 mL/100 mL
INACTIVE INGREDIENTS: WATER; HELIANTHUS ANNUUS (SUNFLOWER) SEED OIL; ROSEMARY; GLYCERIN; ISOPROPYL ALCOHOL

365 Whole Foods Market Refreshing Spray Hand Sanitizer Bergamot Rain

Drug Facts

Active ingredient

Ethyl Alcohol 62% v/v

Purpose

Antiseptic

Uses

to help reduce bacteria on skin.

Warnings

For external use only. Flammable. Keep away from fire or flame.

When using this product avoid contact with eyes. If eye contact occurs, rinse with water.

Stop use and ask a doctor if skin irritation or redness develops.

Keep out of reach of children. In case of accidental ingestion, seek medical help or contact a Poison Control Center immediately.

Directions

apply 1 to 2 sprays on hands and rub together until dry.

Other information

do not store above 104ºF (40ºC).

Inactive ingredients

water, isopropyl alcohol, fragrance (natural)*, glycerin, helianthus annuus (sunflower) seed oil, rosmarinus officinalis (rosemary) leaf extract.

*COMPLIES WITH ISO 9235, SEE www.wholefoodsmarket.com FOR MORE INFORMATION

Questions, Comments?

- customer.questions@wholefoods.com
- 1-844-936-8255